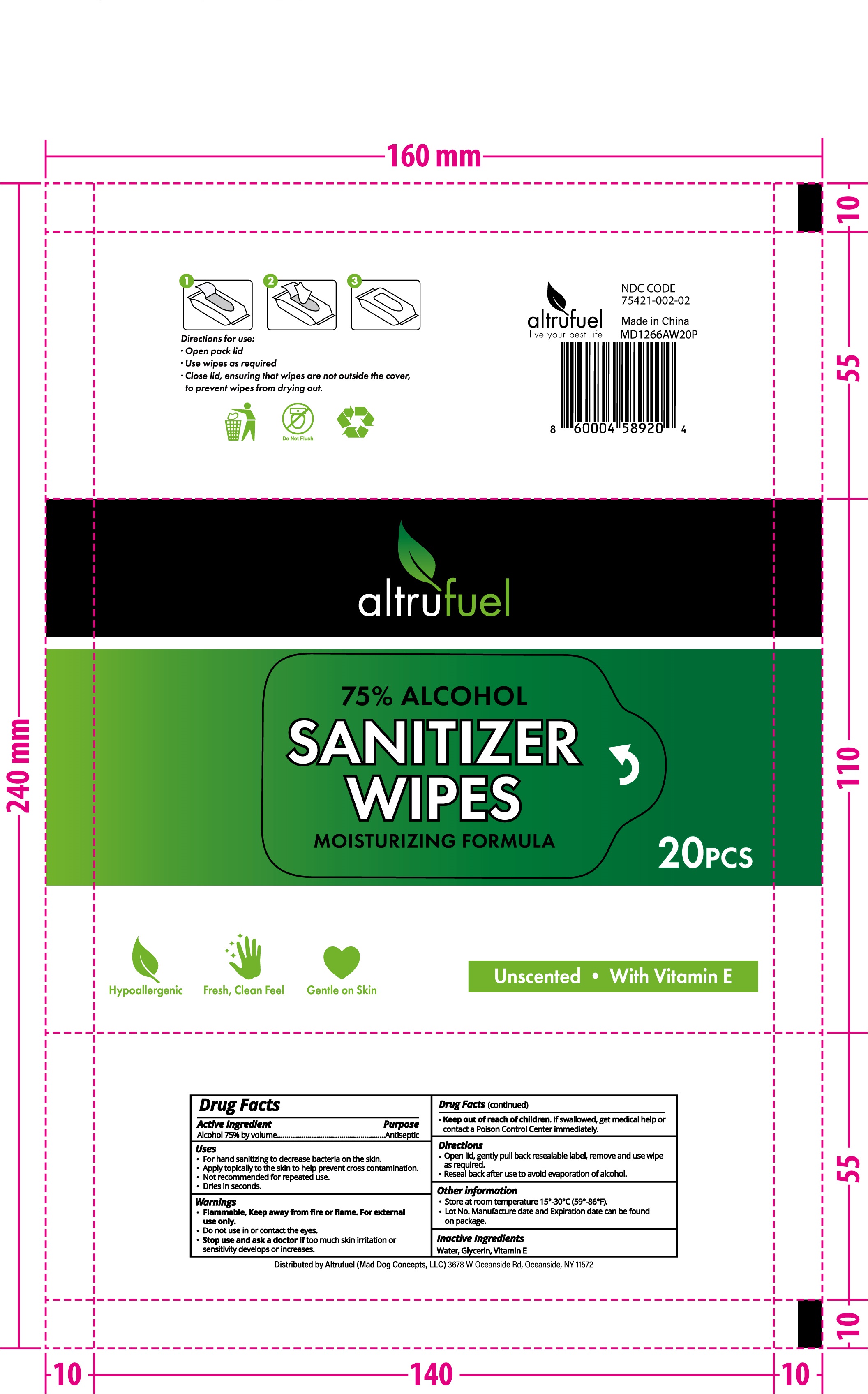 DRUG LABEL: Sanitizer Wipes
NDC: 78536-005 | Form: CLOTH
Manufacturer: Zhejiang Yiwu Mingou Biotechnology Co., Ltd.
Category: otc | Type: HUMAN OTC DRUG LABEL
Date: 20200827

ACTIVE INGREDIENTS: ALCOHOL 75 mL/100 mL
INACTIVE INGREDIENTS: ALPHA-TOCOPHEROL; WATER; GLYCERIN

78536-005 75% Alcohol Instant Sanitizer Wipes

ACTIVE INGREDIENT

Ethyl Alcohol 75%

PURPOSE

Antiseptic

USE

For hand sanitizing to decrease bacteria on the skin.
Apply topically to the skin to help prevent cross contamination.
Not recommended for repeated use.
Dries in seconds.

Warning

Flammable, Keep away from fire or flame. For external
Do not use in or contact the eyes.
Stop use and ask a doctor if too much skin irritation or sensitivity develops or increases.

●Keep out of reach of children. If swallowed, get medical help or contact a Poison Control Center immediately.

Directions

Open lid, gently pull back resealable label, remove and use wipe as required.
Reseal back after use to avoid evaporation of alcohol.

Inactive ingredients

Water, Glycerin, Vitamin E